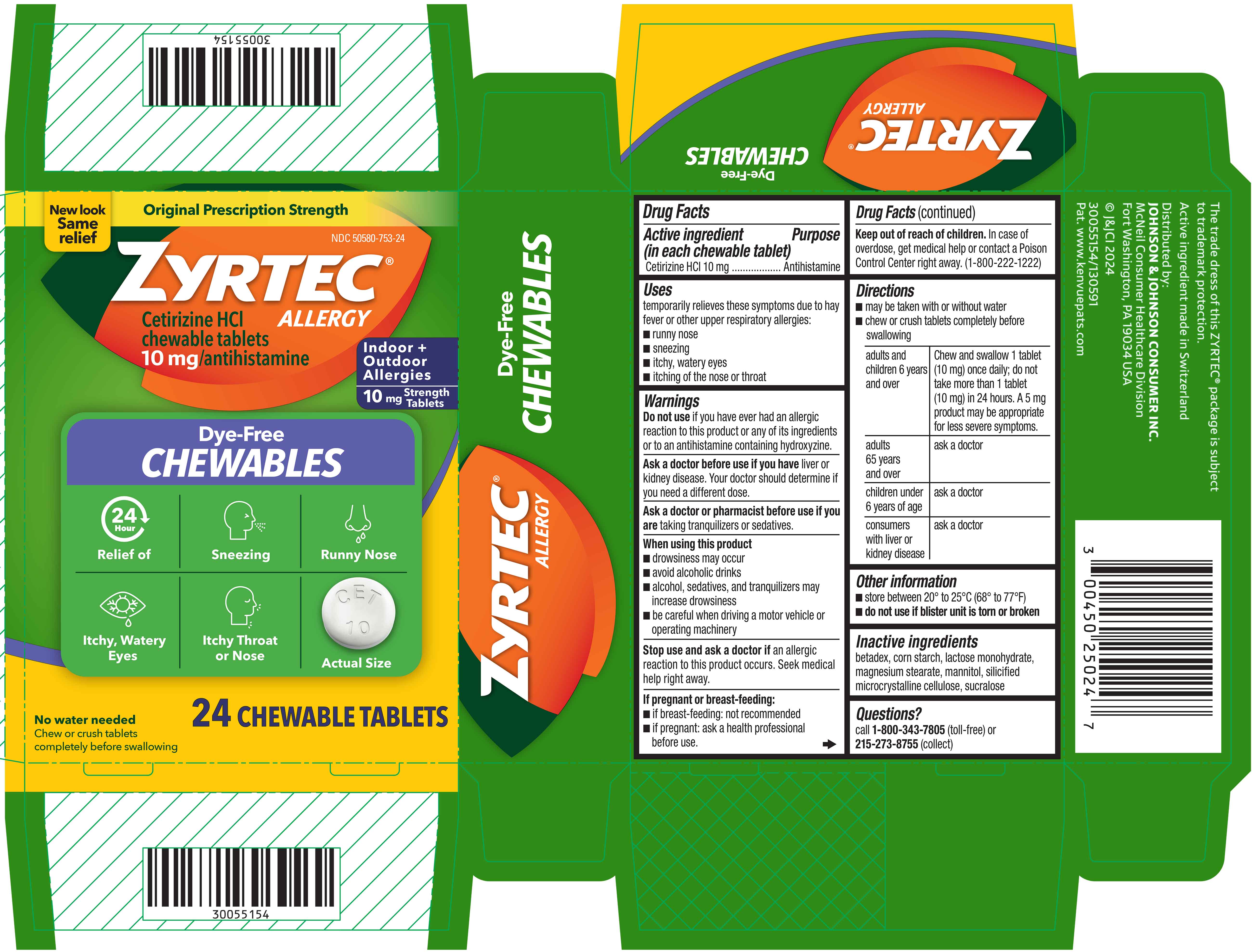 DRUG LABEL: Zyrtec
NDC: 50580-753 | Form: TABLET, CHEWABLE
Manufacturer: Kenvue Brands LLC
Category: otc | Type: HUMAN OTC DRUG LABEL
Date: 20250612

ACTIVE INGREDIENTS: CETIRIZINE HYDROCHLORIDE 10 mg/1 1
INACTIVE INGREDIENTS: BETADEX; STARCH, CORN; MAGNESIUM STEARATE; MANNITOL; SUCRALOSE; LACTOSE MONOHYDRATE

Zyrtec Allergy

Drug Facts

Active ingredient (in each tablet)

Cetirizine HCl 10 mg

Purpose

Antihistamine

Uses

temporarily relieves these symptoms due to hay fever or other upper respiratory allergies:

- runny nose
- sneezing
- itchy, watery eyes
- itching of the nose or throat

Warnings

Do not use if you have ever had an allergic reaction to this product or any of its ingredients or to an antihistamine containing hydroxyzine.

Ask a doctor before use if you have liver or kidney disease. Your doctor should determine if you need a different dose.

Ask a doctor or pharmacist before use if you are taking tranquilizers or sedatives.

When using this product

- drowsiness may occur
- avoid alcoholic drinks
- alcohol, sedatives, and tranquilizers may increase drowsiness
- be careful when driving a motor vehicle or operating machinery

Stop use and ask a doctor if an allergic reaction to this product occurs. Seek medical help right away.

If pregnant or breast-feeding:

- if breast-feeding: not recommended
- if pregnant: ask a health professional before use.

Keep out of reach of children. In case of overdose, get medical help or contact a Poison Control Center right away. (1-800-222-1222)

Directions

- may be taken with or without water
- chew or crush tablets completely before swallowing
  adults and children 6 years and over | Chew and swallow 1 tablet (10 mg) once daily; do not take more than 1 tablet (10 mg) in 24 hours. A 5 mg product may be appropriate for less severe symptoms.
  adults 65 years and over | ask a doctor
  children under 6 years of age | ask a doctor
  consumers with liver or kidney disease | ask a doctor

Other information

- store between 20° to 25°C (68° to 77°F)
- do not use if blister unit is torn or broken

Inactive ingredients

betadex, corn starch, lactose monohydrate, magnesium stearate, mannitol, silicified microcrystalline cellulose, sucralose

Questions?

call 1-800-343-7805 (toll-free) or 215-273-8755 (collect)

PRINCIPAL DISPLAY PANEL

New look

Same

relief

Original Prescription Strength

NDC 50580-753-24

ZYRTEC®

Cetirizine HCl Chewable tablets,
10 mg /antihistamine

ALLERGY

Indoor +

Outdoor

Allergies

10 mg Strength Tablets

Dye-Free

CHEWABLES

24 HOUR

Relief of

- Sneezing
- Runny Nose
- Itchy, Watery Eyes
- Itchy Throat or Nose

Actual Size

No Water Needed

Chew or crush tablets

completely before swallowing

24 Chewable Tablets